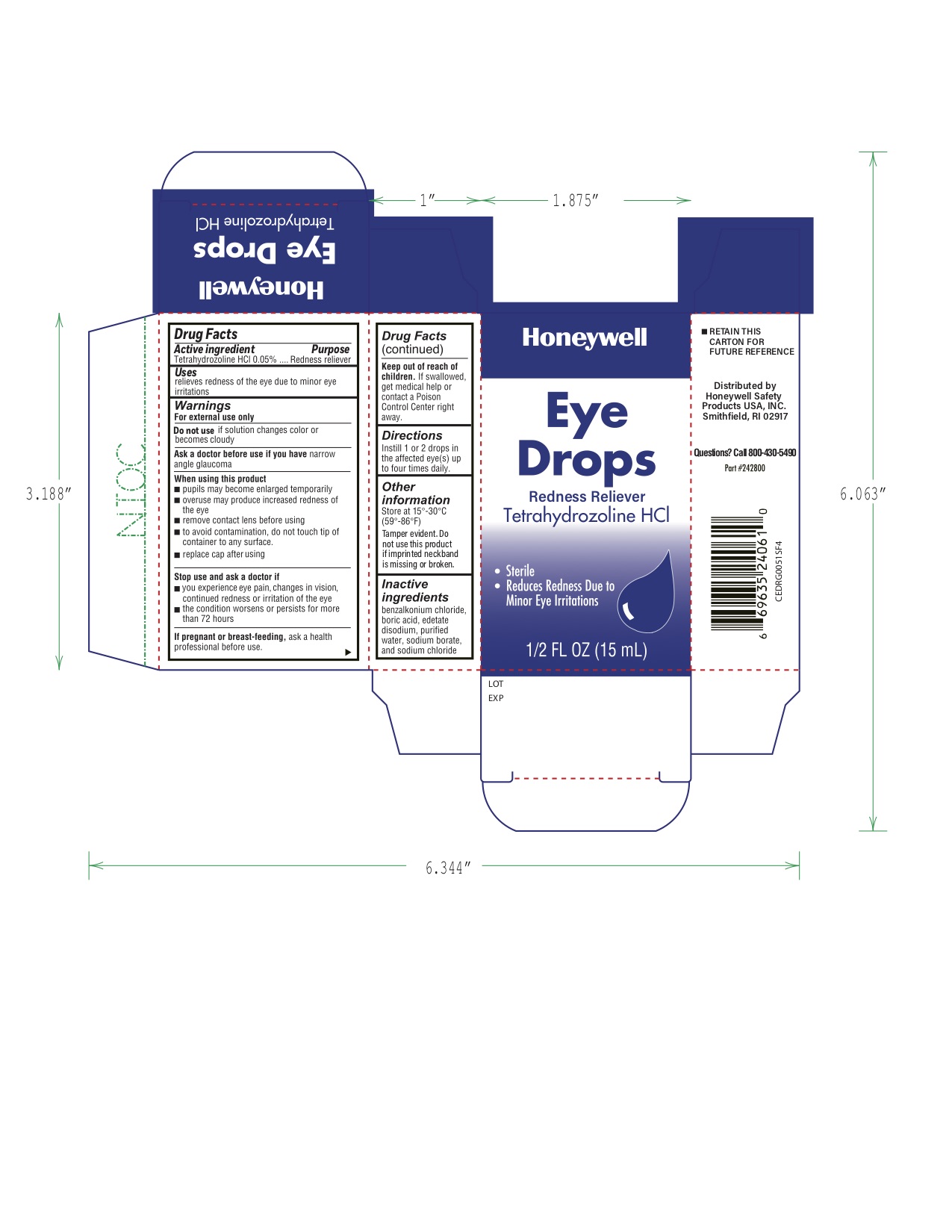 DRUG LABEL: Eye Drops
NDC: 0498-0161 | Form: SOLUTION/ DROPS
Manufacturer: Honeywell Safety Products USA, INC
Category: otc | Type: HUMAN OTC DRUG LABEL
Date: 20240122

ACTIVE INGREDIENTS: TETRAHYDROZOLINE HYDROCHLORIDE 0.05 g/100 mL
INACTIVE INGREDIENTS: BENZALKONIUM CHLORIDE; BORIC ACID; EDETATE DISODIUM; WATER; SODIUM BORATE; SODIUM CHLORIDE

0498-0161: Eye Drops

Drug Facts

Active ingredient

Tetrahydrozoline HCl 0.05%

Purpose

Redness reliever

Uses

relieves redness of the eye due to minor eye irritations

Warnings

For external use only

Do not use if solution changes color or becomes cloudy

Ask a doctor before use if you have narrow angle glaucoma

When using this product

- pupils may become enlarged temporarily
- overuse may produce increased redness of the eye
- remove contact lenses before using
- to avoid contamination, do not touch tip of container to any surface
- replace cap after using

Stop use and ask a doctor if

- you experience eye pain, changes in vision, continued redness or irritation of the eye
- the condition worsens or persists for more than 72 hours

PREGNANCY OR BREAST FEEDING

If pregnant or breast-feeding, ask a health professional before use.

Keep out of reach of children. If swallowed, get medical help or contact a Poison Control Center right away.

Directions

Instill 1 or 2 drops in the affected eye(s) up to four times daily.

Other information Store at 15° to 30°C (59° to 86°F)

INACTIVE INGREDIENT

Inactive ingredients benzalkonium chloride, boric acid, edetate disodium, purified water, sodium borate, sodium chloride

- Tamper evident. Do not use this product if imprinted neckband is missing or broken.
- RETAIN THIS CARTON FOR FUTURE REFERENCE

Distributed by

North by Honeywell

900 Douglas Pike

Smithfield, RI 02917

Questions? Call 800-430-5490